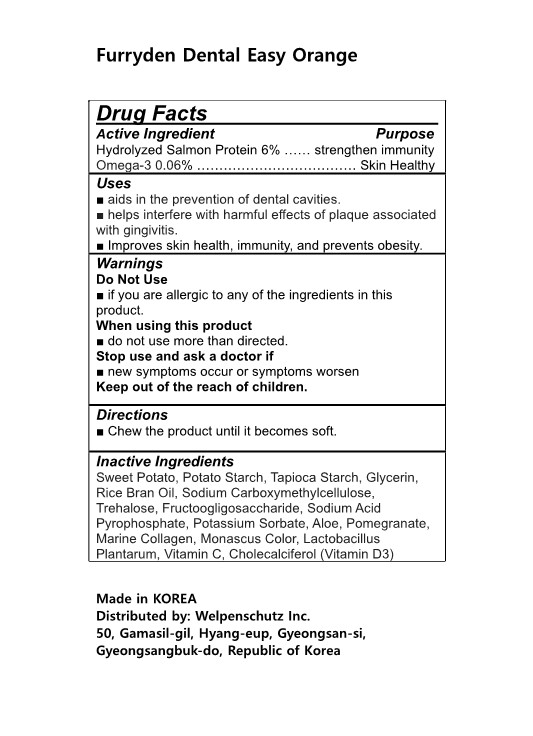 DRUG LABEL: Furryden Dental Easy Orange
NDC: 83332-301 | Form: GUM, CHEWING
Manufacturer: Welpenschutz Inc.
Category: otc | Type: HUMAN OTC DRUG LABEL
Date: 20230209

ACTIVE INGREDIENTS: SALMON, UNSPECIFIED 6 g/100 mL; OMEGA-3 FATTY ACIDS 0.06 g/100 mL
INACTIVE INGREDIENTS: RICE BRAN OIL; CARBOXYMETHYLCELLULOSE SODIUM; TREHALOSE; SODIUM ACID PYROPHOSPHATE; STARCH, TAPIOCA; ALOE; POTASSIUM SORBATE; STARCH, POTATO; SWEET POTATO; LACTIPLANTIBACILLUS PLANTARUM; CHOLECALCIFEROL; POMEGRANATE; FRUCTOSE; MONASCUS PURPUREUS; GLYCERIN; HYDROLYSED MARINE COLLAGEN (ENZYMATIC; 2000 MW); ASCORBIC ACID

83332-301 Furryden Dental Easy Orange

Active Ingredients

Hydrolyzed Salmon Protein 6%

Omega-3 0.06%

Purposes

Hydrolyzed Salmon Protein 6% …… strengthen immunity

Omega-3 0.06% ……………………………… Skin Healthy

Uses

■ aids in the prevention of dental cavities.

■ helps interfere with harmful effects of plaque associated with gingivitis.

■ Improves skin health, immunity, and prevents obesity.

Warnings

Do Not Use

■ if you are allergic to any of the ingredients in this product.

When using this product

■ do not use more than directed.

Stop use and ask a doctor if

■ new symptoms occur or symptoms worsen

Keep out of the reach of children.

Warnings

When using this product

■ do not use more than directed.

Warnings

Stop use and ask a doctor if

■ new symptoms occur or symptoms worsen

Warnings

Keep out of the reach of children.

Warnings

Do Not Use

■ if you are allergic to any of the ingredients in this product.

Directions

■ Chew the product until it becomes soft.

Inactive Ingredients

Sweet Potato, Potato Starch, Tapioca Starch, Glycerin, Rice Bran Oil, Sodium Carboxymethylcellulose, Trehalose, Fructoogligosaccharide, Sodium Acid Pyrophosphate, Potassium Sorbate, Aloe, Pomegranate, Marine Collagen, Monascus Color, Lactobacillus Plantarum, Vitamin C, Cholecalciferol (Vitamin D3)